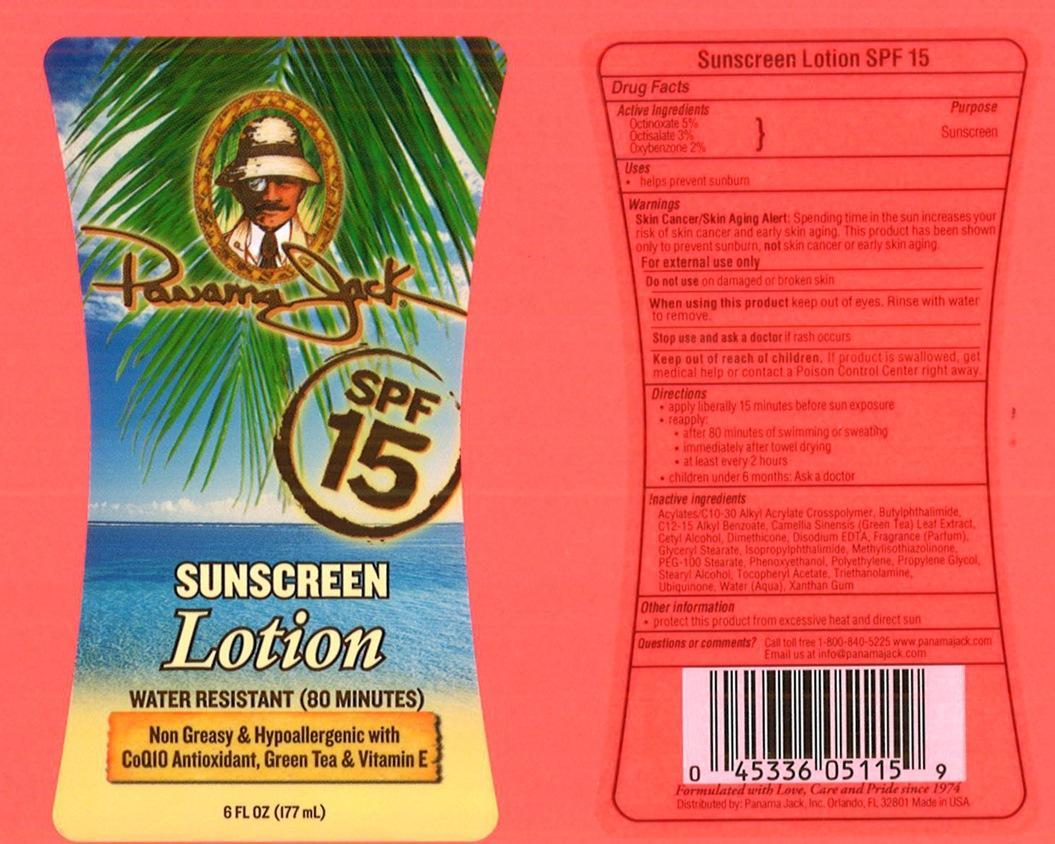 DRUG LABEL: Panama Jack
NDC: 58443-0052 | Form: SPRAY
Manufacturer: Prime Enterprises, Inc.
Category: otc | Type: HUMAN OTC DRUG LABEL
Date: 20200117

ACTIVE INGREDIENTS: OCTINOXATE 48.4 mg/1 mL; OCTISALATE 29 mg/1 mL; OXYBENZONE 19.3 mg/1 mL
INACTIVE INGREDIENTS: CARBOMER COPOLYMER TYPE A (ALLYL PENTAERYTHRITOL CROSSLINKED); 3-BUTYLPHTHALIDE; ISOPROPYLPHTHALIMIDE; ALKYL (C12-15) BENZOATE; CETYL ALCOHOL; DIMETHICONE; GLYCERYL MONOSTEARATE; EDETATE DISODIUM; PEG-100 STEARATE; PHENOXYETHANOL; HIGH DENSITY POLYETHYLENE; PROPYLENE GLYCOL; WATER; GREEN TEA LEAF; STEARYL ALCOHOL; .ALPHA.-TOCOPHEROL ACETATE; TROLAMINE; UBIDECARENONE; METHYLISOTHIAZOLINONE; XANTHAN GUM

Active ingredients

Octinoxate 5 %, Octisalate 3 % and Oxybenzone 2 %

Purpose

Sunscreen

Uses

- helps prevent sunburn

Warnings

Skin Cancer/Skin Aging Alert: Spending time in the sun increases your risk of skin cancer and early skin aging. This product has been shown only to prevent sunburn, not skin cancer or early skin aging.

OTHER SAFETY INFORMATION

For external use only

Do not use on damaged or broken skin.

When using this product keep out of eyes. Rinse with water to remove.

Stop use and ask a doctor if rash occurs.

Keep out of reach of children. If product is swallowed, get medical help or contact a Poison Control Center right away.

Directions

- apply liberally 15 minutes before sun exposure
- reapply
  - after 80 minutes of swimming or sweating
  - immediately after towel drying
  - at least every 2 hours
- children under 6 months: Ask a doctor

Inactive Ingredients

Acrylates/C10-30 Alkyl Acrylate Crosspolymer, Butylphthalimide, C12-15 Alkyl Benzoate, Camellia Sinensis (Green Tea) Leaf Extract, Cetyl Alcohol, Dimethicone, Disodium EDTA, Fragrance (Parfum), Glyceryl Stearate, Isopropylphthalimide, Methylisothiazolinone, PEG-100 Stearate, Phenoxyethanol, Polyethylene, Propylene Glycol, Stearyl Alcohol, Tocopheryl Acetate, Triethanolamine, Ubiquinone, Water (Aqua), Xanthan Gum

Other information

- protect this product from excesive heat and direct sun

Questions or Comments?

Call toll free 1-800-840-5225 www.panamajack.com

Email us at info@panamajack.com

PRINCIPAL DISPLAY PANEL - 177 mL Bottle Label

Panama Jack

SPF 15

SUNSCREEN

Lotion

WATER RESISTANT (80 MINUTES)

Non Greasy & Hypoallergenic with

CoQ10 Antioxidant, Green Tea & Vitamin E

6 FL OZ (177 mL)